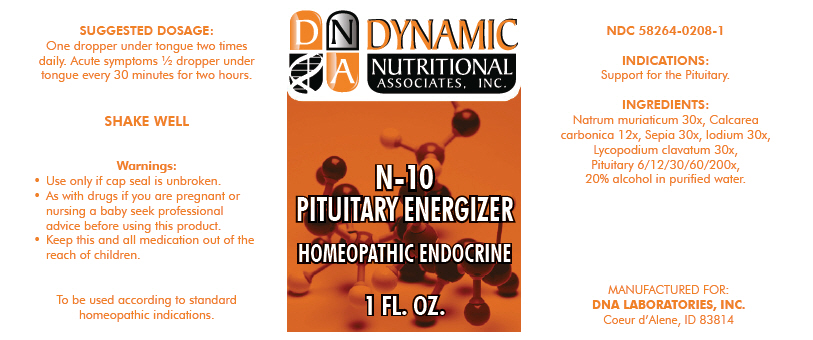 DRUG LABEL: N-10
NDC: 58264-0208 | Form: SOLUTION
Manufacturer: DNA Labs, Inc.
Category: homeopathic | Type: HUMAN OTC DRUG LABEL
Date: 20250109

ACTIVE INGREDIENTS: SODIUM CHLORIDE 30 [hp_X]/1 mL; OYSTER SHELL CALCIUM CARBONATE, CRUDE 12 [hp_X]/1 mL; SEPIA OFFICINALIS JUICE 30 [hp_X]/1 mL; IODINE 30 [hp_X]/1 mL; LYCOPODIUM CLAVATUM WHOLE 30 [hp_X]/1 mL; BOS TAURUS PITUITARY GLAND, POSTERIOR 200 [hp_X]/1 mL
INACTIVE INGREDIENTS: ALCOHOL; WATER

N-10

NDC 58264-0208-1

INDICATIONS

PURPOSE

Support for the Pituitary.

INGREDIENTS

INACTIVE INGREDIENT

Natrum muriaticum 30x, Calcarea carbonica 12x, Sepia 30x, Iodium 30x, Lycopodium clavatum 30x, Pituitary 6/12/30/60/200x, 20% alcohol in purified water.

SUGGESTED DOSAGE

One dropper under tongue two times daily. Acute symptoms ½ dropper under tongue every 30 minutes for two hours.

STORAGE AND HANDLING

SHAKE WELL

Warnings

- Use only if cap seal is unbroken.

PREGNANCY OR BREAST FEEDING

- As with drugs if you are pregnant or nursing a baby seek professional advice before using this product.

KEEP OUT OF REACH OF CHILDREN

- Keep this and all medication out of the reach of children.

To be used according to standard homeopathic indications.

PRINCIPAL DISPLAY PANEL - 1 FL. OZ. Bottle Label

DYNAMIC
NUTRITIONAL
ASSOCIATES, INC.

N-10

PITUITARY ENERGIZER

HOMEOPATHIC ENDOCRINE

1 FL. OZ.